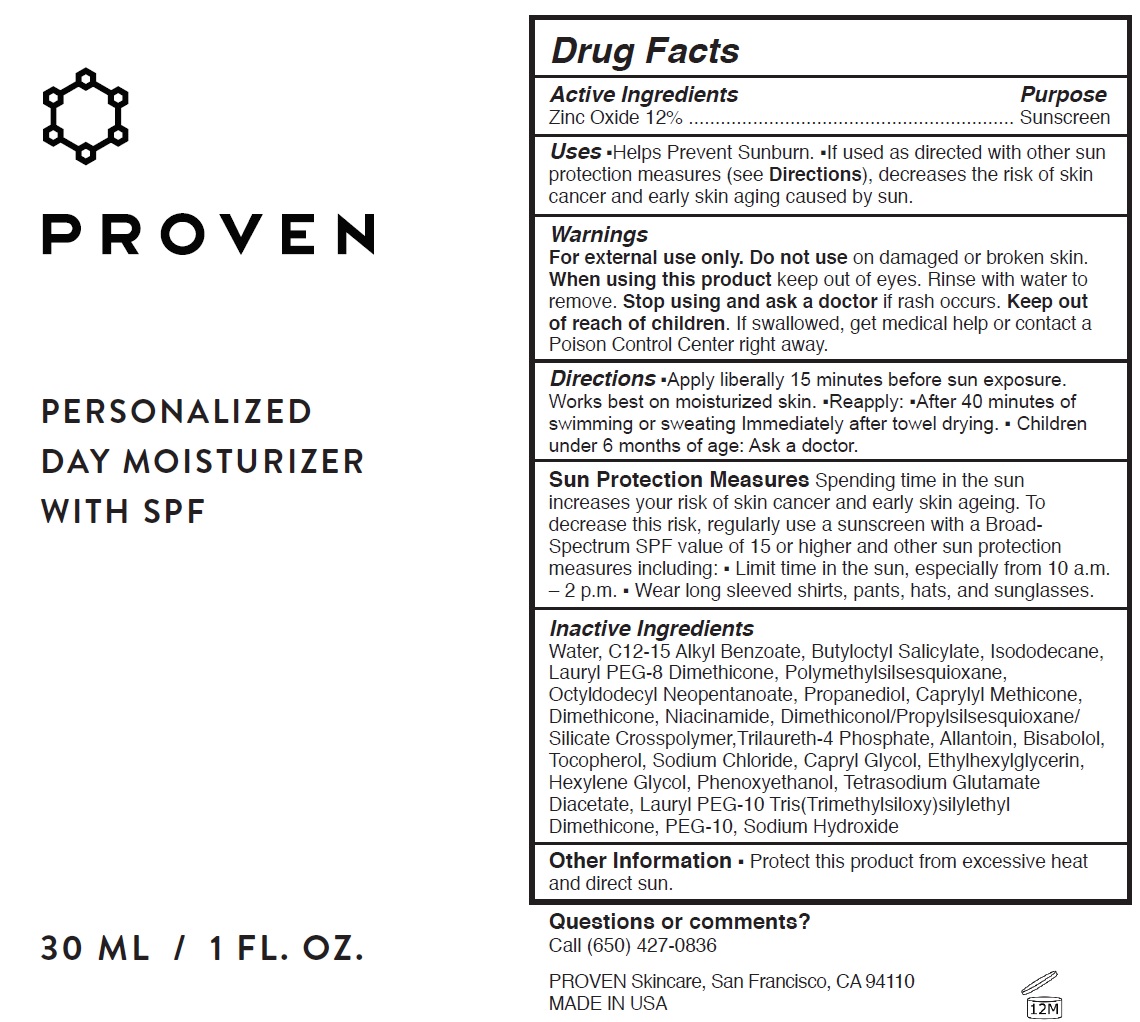 DRUG LABEL: Personalized Day Moisturizer with SPF
NDC: 73572-003 | Form: CREAM
Manufacturer: Proven Skincare
Category: otc | Type: HUMAN OTC DRUG LABEL
Date: 20231110

ACTIVE INGREDIENTS: ZINC OXIDE 120 mg/1 mL
INACTIVE INGREDIENTS: WATER; ALKYL (C12-15) BENZOATE; BUTYLOCTYL SALICYLATE; ISODODECANE; POLYMETHYLSILSESQUIOXANE (4.5 MICRONS); OCTYLDODECYL NEOPENTANOATE; PROPANEDIOL; CAPRYLYL TRISILOXANE; DIMETHICONE; NIACINAMIDE; TRILAURETH-4 PHOSPHATE; ALLANTOIN; LEVOMENOL; TOCOPHEROL; SODIUM CHLORIDE; CAPRYLYL GLYCOL; ETHYLHEXYLGLYCERIN; HEXYLENE GLYCOL; PHENOXYETHANOL; TETRASODIUM GLUTAMATE DIACETATE; POLYETHYLENE GLYCOL 500; SODIUM HYDROXIDE

Personalized Day Moisturizer with SPF (50)

Active Ingredients

Zinc Oxide 12%

Purpose

Sunscreen

Uses

- Helps Prevent Sunburn.
- If used as directed with other sun protection measures (see), decreases the risk of skin cancer and early skin aging caused by sun. Directions

Warnings

For external use only.

Do not use

on damaged or broken skin.

When using this product

keep out of eyes. Rinse with water to remove.

Stop using and ask a doctor

if rash occurs.

Keep out of reach of children.

If swallowed, get medical help or contact a Poison Control Center right away.

Directions

- Apply liberally 15 minutes before sun exposure. Works best on moisturized skin.
- Reapply:
- After 40 minutes of swimming or sweating Immediately after towel drying.
- Children under 6 months of age: Ask a doctor.

- Limit time in the sun, especially from 10 a.m. – 2 p.m.
- Wear long sleeved shirts, pants, hats, and sunglasses.

Spending time in the sun increases your risk of skin cancer and early skin ageing. To decrease this risk, regularly use a sunscreen with a Broad- Spectrum SPF value of 15 or higher and other sun protection measures including: Sun Protection Measures

Inactive Ingredients

Water, C12-15 Alkyl Benzoate, Butyloctyl Salicylate, Isododecane, Lauryl PEG-8 Dimethicone, Polymethylsilsesquioxane, Octyldodecyl Neopentanoate, Propanediol, Caprylyl Methicone, Dimethicone, Niacinamide, Dimethiconol/Propylsilsesquioxane/ Silicate Crosspolymer,Trilaureth-4 Phosphate, Allantoin, Bisabolol, Tocopherol, Sodium Chloride, Capryl Glycol, Ethylhexylglycerin, Hexylene Glycol, Phenoxyethanol, Tetrasodium Glutamate Diacetate, Lauryl PEG-10 Tris(Trimethylsiloxy)silylethyl Dimethicone, PEG-10, Sodium Hydroxide

Other Information

- Protect this product from excessive heat and direct sun.